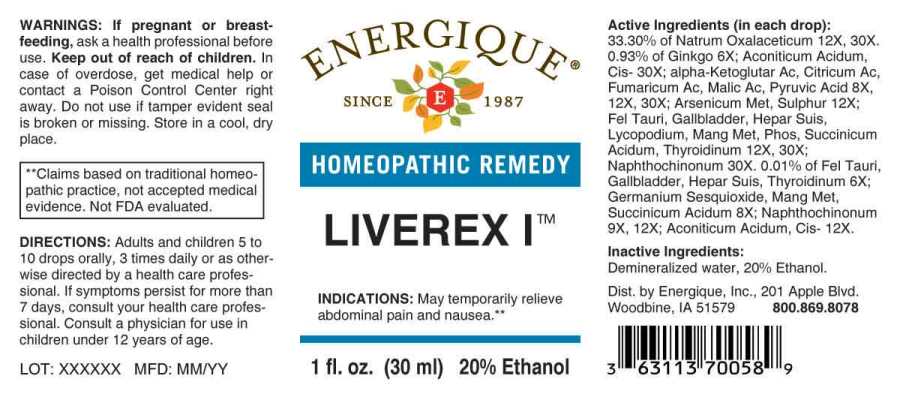 DRUG LABEL: Liverex I
NDC: 44911-0419 | Form: LIQUID
Manufacturer: Energique, Inc.
Category: homeopathic | Type: HUMAN OTC DRUG LABEL
Date: 20230721

ACTIVE INGREDIENTS: GINKGO 6 [hp_X]/1 mL; BOS TAURUS BILE 6 [hp_X]/1 mL; SUS SCROFA GALLBLADDER 6 [hp_X]/1 mL; PORK LIVER 6 [hp_X]/1 mL; THYROID 6 [hp_X]/1 mL; GERMANIUM SESQUIOXIDE 8 [hp_X]/1 mL; OXOGLURIC ACID 8 [hp_X]/1 mL; ANHYDROUS CITRIC ACID 8 [hp_X]/1 mL; FUMARIC ACID 8 [hp_X]/1 mL; MALIC ACID 8 [hp_X]/1 mL; MANGANESE 8 [hp_X]/1 mL; PYRUVIC ACID 8 [hp_X]/1 mL; SUCCINIC ACID 8 [hp_X]/1 mL; 1,4-NAPHTHOQUINONE 9 [hp_X]/1 mL; ARSENIC 12 [hp_X]/1 mL; SULFUR 12 [hp_X]/1 mL; ACONITIC ACID, (Z)- 12 [hp_X]/1 mL; LYCOPODIUM CLAVATUM SPORE 12 [hp_X]/1 mL; SODIUM DIETHYL OXALACETATE 12 [hp_X]/1 mL; PHOSPHORUS 12 [hp_X]/1 mL
INACTIVE INGREDIENTS: WATER; ALCOHOL

DRUG FACTS:

ACTIVE INGREDIENTS:

(in each drop): 33.30% of Natrum Oxalaceticum 12X, 30X. 0.93% of Ginkgo Biloba 6X; Aconiticum Acidum, Cis 30X; Alpha-Ketoglutaricum Acidum 8X, 12X, 30X, Citricum Acidum 8X, 12X, 30X, Fumaricum Acidum 8X, 12X, 30X, Malicum Acidum 8X, 12X, 30X, Pyruvic Acid 8X, 12X, 30X; Arsenicum Metallicum 12X, Sulphur 12X; Fel Tauri 12X, 30X, Gallbladder (Suis) 12X, 30X, Hepar Suis 12X, 30X, Lycopodium Clavatum 12X, 30X, Manganum Metallicum 12X, 30X, Phosphorus 12X, 30X, Succinicum Acidum 12X, 30X, Thyroidinum (Suis) 12X, 30X; Naphthochinonum 30X. 0.01% of Fel Tauri 6X, Gallbladder (Suis) 6X, Hepar Suis 6X, Thyroidinum (Suis) 6X; Germanium Sesquioxide 8X, Manganum Metallicum 8X, Succinicum Acidum 8X; Naphthochinonum 9X, 12X; Aconiticum Acidum, Cis 12X.

INDICATIONS:

May temporarily relieve abdominal pain and nausea.**

**Claims based on traditional homeopathic practice, not accepted medical evidence. Not FDA evaluated.

WARNINGS:

If pregnant or breastfeeding, ask a health professional before use.

Keep out of reach of children. In case of overdose, get medical help or contact a Poison Control Center right away.

Do not use if tamper evident seal is broken or missing.

Store in a cool, dry place.

Keep out of reach of children. In case of overdose, get medical help or contact a Poison Control Center right away.

DIRECTIONS:

Adults and children 5 to 10 drops orally, 3 times daily or as otherwise directed by a health care professional. If symptoms persist for more than 7 days, consult your health care professional. Consult a physician for use in children under 12 years of age.

INDICATIONS:

May temporarily relieve abdominal pain and nausea.**

**Claims based on traditional homeopathic practice, not accepted medical evidence. Not FDA evaluated.

INACTIVE INGREDIENTS:

Demineralized water, 20% Ethanol.

QUESTIONS:

Dist. by Energique, Inc.
201 Apple Blvd.
Woodbine, IA 51579 800.869.8078

PACKAGE LABEL DISPLAY:

ENERGIQUE

SINCE 1987

HOMEOPATHIC REMEDY

LIVEREX I

1fl. oz. (30 ml)